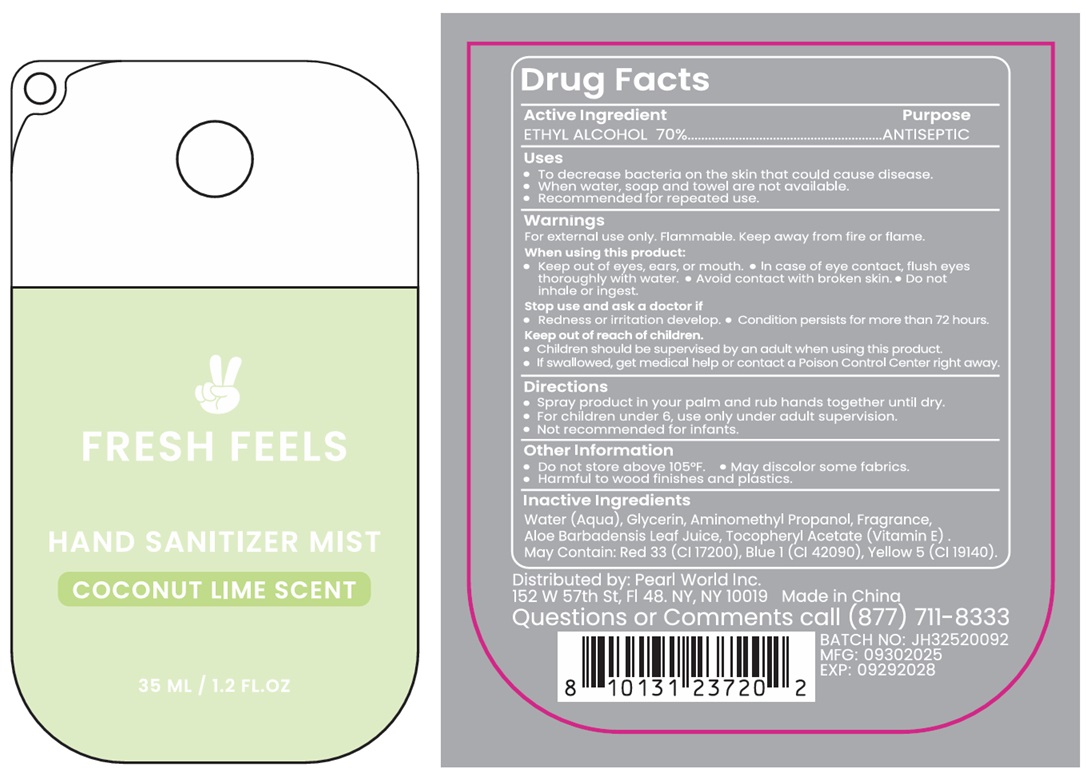 DRUG LABEL: FRESH FEELS HAND SANITIZER MIST COCONUT LIME SCENT
NDC: 69933-116 | Form: SPRAY
Manufacturer: Pearl World Inc.
Category: otc | Type: HUMAN OTC DRUG LABEL
Date: 20251006

ACTIVE INGREDIENTS: ALCOHOL 70 mL/100 mL
INACTIVE INGREDIENTS: WATER; GLYCERIN; AMINOMETHYLPROPANOL; ALOE VERA LEAF JUICE; .ALPHA.-TOCOPHEROL ACETATE; D&C RED NO. 33; FD&C BLUE NO. 1; FD&C YELLOW NO. 5

FRESH FEELS HAND SANITIZER MIST COCONUT LIME SCENT

Active Ingredient

ETHYL ALCOHOL 70%

Purpose

ANTISEPTIC

Uses

• To decrease bacteria on the skin that could cause disease.
• When water, soap and towel are not available.
• Recommended for repeated use.

Warnings

For external use only. Flammable. Keep away from fire or flame.

When using this product:
• Keep out of eyes, ears, or mouth. • In case of eye contact, flush eyes thoroughly with water. • Avoid contact with broken skin. • Do not inhale or ingest.

Stop use and ask a doctor if
• Redness or irritation develop. • Condition persists for more than 72 hours.

Keep out of reach of children.
• Children should be supervised by an adult when using this product.
• If swallowed, get medical help or contact a Poison Control Center right away.

Directions

• Spray product in your palm and rub hands together until dry.
• For children under 6, use only under adult supervision.
• Not recommended for infants.

Other Information

• Do not store above 105°F. • May discolor some fabrics.
• Harmful to wood finishes and plastics.

Inactive Ingredients

Water (Aqua), Glycerin, Aminomethyl Propanol, Fragrance, Aloe Barbadensis Leaf Juice, Tocopheryl Acetate (Vitamin E).
May Contain: Red 33 (CI 17200), Blue 1 (CI 42090), Yellow 5 (CI 19140).

Distributed by: Pearl World Inc.
152 W 57th St, Fl 48. NY, NY 10019

Made in China

Questions or Comments call (877) 711-8333